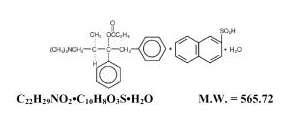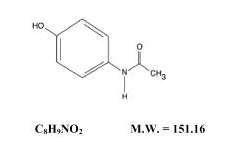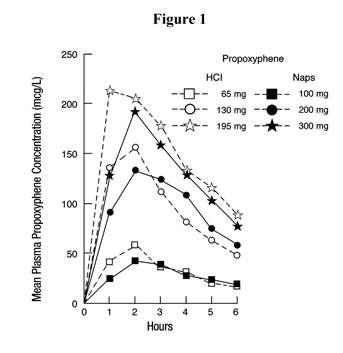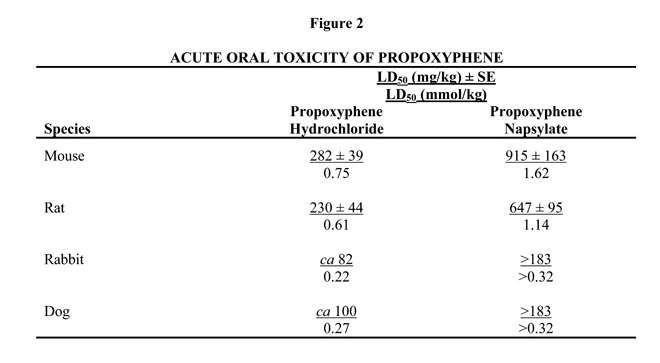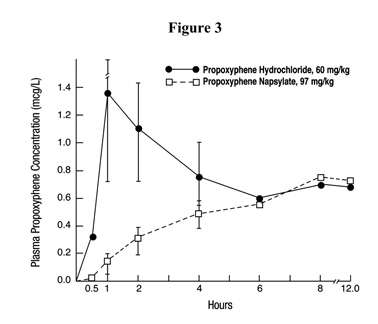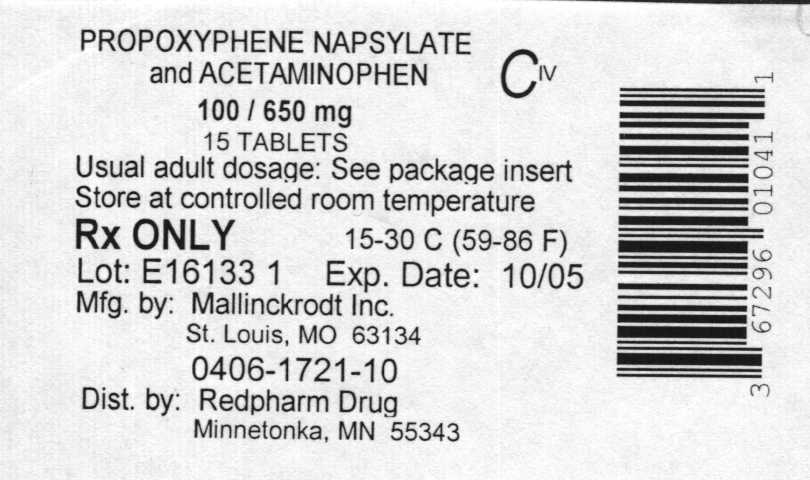 DRUG LABEL: PROPOXYPHENE NAPSYLATE AND ACETAMINOPHEN
NDC: 67296-0105 | Form: TABLET
Manufacturer: RedPharm Drug Inc.
Category: prescription | Type: HUMAN PRESCRIPTION DRUG LABEL
Date: 20110620
DEA Schedule: CIV

ACTIVE INGREDIENTS: PROPOXYPHENE NAPSYLATE 100 mg/1 1; ACETAMINOPHEN 650 mg/1 1
INACTIVE INGREDIENTS: CROSPOVIDONE; HYPROMELLOSES; MAGNESIUM STEARATE; CELLULOSE, MICROCRYSTALLINE; POLYDEXTROSE; POLYETHYLENE GLYCOLS; POVIDONE; STARCH, CORN; SILICON DIOXIDE; STEARIC ACID; TITANIUM DIOXIDE; TRIACETIN; D&C RED NO. 27; FD&C YELLOW NO. 6; ALUMINUM OXIDE

Propoxyphene Napsylate and Acetaminophen Tablets

DESCRIPTION

Propoxyphene napsylate USP is an odorless, white crystalline powder with a bitter taste. It is very slightly soluble in water and soluble in methanol, ethanol, chloroform, and acetone. Chemically, it is (αS,1R)-α-[2-(Dimethylamino)-1-methylethyl]-α-phenylphenethyl propionate compound with 2-naphthalenesulfonic acid (1:1) monohydrate, which can be represented by the accompanying structural formula:
Propoxyphene napsylate differs from propoxyphene hydrochloride in that it allows more stable liquid dosage forms and tablet formulations. Because of differences in molecular weight, a dose of 100 mg (176.8 μmol) of propoxyphene napsylate is required to supply an amount of propoxyphene equivalent to that present in 65 mg (172.9 μmol) of propoxyphene hydrochloride.
The acetaminophen component is 4′-Hydroxyacetanilide, a white, odorless, crystalline powder possessing a slightly bitter taste, and is represented by the following structural formula:
Each tablet of Propoxyphene Napsylate and Acetaminophen Tablets USP, for oral administration, contains 100 mg (176.8 μmol) propoxyphene napsylate and 650 mg (4,300 μmol) acetaminophen.
Each pink tablet also contains crospovidone, D and C Red No. 27 Aluminum Lake, FD and C Yellow No. 6 Aluminum Lake, hydroxypropyl methylcellulose, magnesium stearate, microcrystalline cellulose, polydextrose, polyethylene glycol, povidone, pregelatinized starch, silicon dioxide, stearic acid, titanium dioxide, and triacetin.
Each white tablet also contains crospovidone, hydroxypropyl methylcellulose, magnesium stearate, microcrystalline cellulose, polydextrose, polyethylene glycol, povidone, pregelatinized starch, silicon dioxide, stearic acid, titanium dioxide, and triacetin.

CLINICAL PHARMACOLOGY

Propoxyphene is a centrally acting narcotic analgesic agent. Equimolar doses of propoxyphene hydrochloride or napsylate provide similar plasma concentrations. Following administration of 65, 130, or 195 mg of propoxyphene hydrochloride, the bioavailability of propoxyphene is equivalent to that of 100, 200, or 300 mg respectively of propoxyphene napsylate. Peak plasma concentrations of propoxyphene are reached in 2 to 2 1/2 hours. After a 100 mg oral dose of propoxyphene napsylate, peak plasma levels of 0.05 to 0.1 mcg/mL are achieved. As shown in Figure 1, the napsylate salt tends to be absorbed more slowly than the hydrochloride. At or near therapeutic doses, this absorption difference is small when compared with that among subjects and among doses.
Figure 1. Mean plasma concentrations of propoxyphene in 8 human subjects following oral administration of 65 and 130 mg of the hydrochloride salt and 100 and 200 mg of the napsylate salt and in 7 given 195 mg of the hydrochloride and 300 mg of the napsylate salt.
Because of this several hundredfold difference in solubility, the absorption rate of very large doses of the napsylate salt is significantly lower than that of equimolar doses of the hydrochloride.
Repeated doses of propoxyphene at 6-hour intervals lead to increasing plasma concentrations, with a plateau after the ninth dose at 48 hours.
Propoxyphene is metabolized in the liver to yield norpropoxyphene. Propoxyphene has a half-life of 6 to 12 hours, whereas that of norpropoxyphene is 30 to 36 hours.
Norpropoxyphene has substantially less central-nervous-system-depressant effect than propoxyphene but a greater local anesthetic effect, which is similar to that of amitriptyline and antiarrhythmic agents, such as lidocaine and quinidine.
In animal studies in which propoxyphene and norpropoxyphene were continuously infused in large amounts, intracardiac conduction time (PR and QRS intervals) was prolonged. Any intracardiac conduction delay attributable to high concentrations of norpropoxyphene may be of relatively long duration.
Actions

Propoxyphene is a mild narcotic analgesic structurally related to methadone. The potency of propoxyphene napsylate is from two thirds to equal that of codeine.
Propoxyphene napsylate and acetaminophen tablets provide the analgesic activity of propoxyphene napsylate and the antipyretic-analgesic activity of acetaminophen.
The combination of propoxyphene and acetaminophen produces greater analgesia than that produced by either propoxyphene or acetaminophen administered alone.

INDICATIONS AND USAGE

This product is indicated for the relief of mild to moderate pain, either when pain is present alone or when it is accompanied by fever.

CONTRAINDICATIONS

Hypersensitivity to propoxyphene or acetaminophen.

WARNINGS

- Do not prescribe propoxyphene for patients who are suicidal or addiction-prone.
- Prescribe propoxyphene with caution for patients taking tranquilizers or antidepressant drugs and patients who use alcohol in excess.
- Tell your patients not to exceed the recommended dose and to limit their intake of alcohol.

Propoxyphene products in excessive doses, either alone or in combination with other CNS depressants, including alcohol, are a major cause of drug-related deaths. Fatalities within the first hour of overdosage are not uncommon. In a survey of deaths due to overdosage conducted in 1975, in approximately 20% of the fatal cases, death occurred within the first hour (5% occurred within 15 minutes). Propoxyphene should not be taken in doses higher than those recommended by the physician. The judicious prescribing of propoxyphene is essential to the safe use of this drug. With patients who are depressed or suicidal, consideration should be given to the use of non-narcotic analgesics. Patients should be cautioned about the concomitant use of propoxyphene products and alcohol because of potentially serious CNS-additive effects of these agents. Because of its added depressant effects, propoxyphene should be prescribed with caution for those patients whose medical condition requires the concomitant administration of sedatives, tranquilizers, muscle relaxants, antidepressants, or other CNS-depressant drugs. Patients should be advised of the additive depressant effects of these combinations.
Many of the propoxyphene-related deaths have occurred in patients with previous histories of emotional disturbances or suicidal ideation or attempts as well as histories of misuse of tranquilizers, alcohol, and other CNS-active drugs. Some deaths have occurred as a consequence of the accidental ingestion of excessive quantities of propoxyphene alone or in combination with other drugs. Patients taking propoxyphene should be warned not to exceed the dosage recommended by the physician.

Usage in Ambulatory Patients

Propoxyphene may impair the mental and/or physical abilities required for the performance of potentially hazardous tasks, such as driving a car or operating machinery. The patient should be cautioned accordingly.

PRECAUTIONS

General

Propoxyphene should be administered with caution to patients with hepatic or renal impairment since higher serum concentrations or delayed elimination may occur.

Information for Patients

See accompanying Patient Information Sheet.

Drug Interactions

The CNS-depressant effect of propoxyphene is additive with that of other CNS depressants, including alcohol.
As is the case with many medicinal agents, propoxyphene may slow the metabolism of a concomitantly administered drug. Should this occur, the higher serum concentrations of that drug may result in increased pharmacologic or adverse effects of that drug. Such occurrences have been reported when propoxyphene was administered to patients on antidepressants, anticonvulsants, or warfarin-like drugs. Severe neurologic signs, including coma, have occurred with concurrent use of carbamazepine.

Pregnancy

Safe use in pregnancy has not been established relative to possible adverse effects on fetal development. Instances of withdrawal symptoms in the neonate have been reported following usage during pregnancy. Therefore, propoxyphene should not be used in pregnant women unless, in the judgment of the physician, the potential benefits outweigh the possible hazards.

Nursing Mothers

Low levels of propoxyphene have been detected in human milk. In postpartum studies involving nursing mothers who were given propoxyphene, no adverse effects were noted in infants receiving mother’s milk.

Pediatric Use

Safety and effectiveness in pediatric patients have not been established.

Geriatric Use

The rate of propoxyphene metabolism may be reduced in some patients. Increased dosing interval should be considered.

ADVERSE REACTIONS

In a survey conducted in hospitalized patients, less than 1% of patients taking propoxyphene hydrochloride at recommended doses experienced side effects. The most frequently reported were dizziness, sedation, nausea, and vomiting. Some of these adverse reactions may be alleviated if the patient lies down.
Other adverse reactions include constipation, abdominal pain, skin rashes, lightheadedness, headache, weakness, euphoria, dysphoria, hallucinations, and minor visual disturbances.
Liver dysfunction has been reported in association with both active components of propoxyphene napsylate and acetaminophen tablets. Propoxyphene therapy has been associated with abnormal liver function tests and, more rarely, with instances of reversible jaundice (including cholestatic jaundice). Hepatic necrosis may result from acute overdose of acetaminophen (see OVERDOSAGE). In chronic ethanol abusers, this has been reported rarely with short-term use of acetaminophen dosages of 2.5 to 10 g/day. Fatalities have occurred.
Renal papillary necrosis may result from chronic acetaminophen use, particularly when the dosage is greater than recommended and when combined with aspirin.
Subacute painful myopathy has occurred following chronic propoxyphene overdosage.

DRUG ABUSE AND DEPENDENCE

Propoxyphene, when taken in higher-than-recommended doses over long periods of time, can produce drug dependence characterized by psychic dependence and, less frequently, physical dependence and tolerance. Propoxyphene will only partially suppress the withdrawal syndrome in individuals physically dependent on morphine or other narcotics. The abuse liability of propoxyphene is qualitatively similar to that of codeine although quantitatively less, and propoxyphene should be prescribed with the same degree of caution appropriate to the use of codeine.

OVERDOSAGE

In all cases of suspected overdosage, call your regional Poison Control Center to obtain the most up-to-date information about the treatment of overdose. This recommendation is made because, in general, information regarding the treatment of overdosage may change more rapidly than do package inserts.
Initial consideration should be given to the management of the CNS effects of propoxyphene overdosage. Resuscitative measures should be initiated promptly.

Symptoms of Propoxyphene Overdosage

The manifestations of acute overdosage with propoxyphene are those of narcotic overdosage. The patient is usually somnolent but may be stuporous or comatose and convulsing. Respiratory depression is characteristic. The ventilatory rate and/or tidal volume is decreased, which results in cyanosis and hypoxia. Pupils, initially pinpoint, may become dilated as hypoxia increases. Cheyne-Stokes respiration and apnea may occur. Blood pressure and heart rate are usually normal initially, but blood pressure falls and cardiac performance deteriorates, which ultimately results in pulmonary edema and circulatory collapse, unless the respiratory depression is corrected and adequate ventilation is restored promptly. Cardiac arrhythmias and conduction delay may be present. A combined respiratory-metabolic acidosis occurs owing to retained CO2 (hypercapnia) and to lactic acid formed during anaerobic glycolysis. Acidosis may be severe if large amounts of salicylates have also been ingested. Death may occur.

Treatment of Propoxyphene Overdosage

Attention should be directed first to establishing a patent airway and to restoring ventilation. Mechanically assisted ventilation, with or without oxygen, may be required, and positive pressure respiration may be desirable if pulmonary edema is present. The narcotic antagonist naloxone will markedly reduce the degree of respiratory depression, and 0.4 to 2 mg should be administered promptly, preferably intravenously. If the desired degree of counteraction with improvement in respiratory functions is not obtained, naloxone should be repeated at 2- to 3-minute intervals. The duration of action of the antagonist may be brief. If no response is observed after 10 mg of naloxone have been administered, the diagnosis of propoxyphene toxicity should be questioned. Naloxone may also be administered by continuous intravenous infusion.

Treatment of Propoxyphene Overdosage in Pediatric Patients

The usual initial dose of naloxone in pediatric patients is 0.01 mg/kg body weight given intravenously. If this dose does not result in the desired degree of clinical improvement, a subsequent increased dose of 0.1 mg/kg body weight may be administered. If an IV route of administration is not available, naloxone may be administered IM or subcutaneously in divided doses. If necessary, naloxone can be diluted with Sterile Water for Injection.
Blood gases, pH, and electrolytes should be monitored in order that acidosis and any electrolyte disturbance present may be corrected promptly. Acidosis, hypoxia, and generalized CNS depression predispose to the development of cardiac arrhythmias. Ventricular fibrillation or cardiac arrest may occur and necessitate the full complement of cardiopulmonary resuscitation (CPR) measures. Respiratory acidosis rapidly subsides as ventilation is restored and hypercapnia eliminated, but lactic acidosis may require intravenous bicarbonate for prompt correction.
Electrocardiographic monitoring is essential. Prompt correction of hypoxia, acidosis, and electrolyte disturbance (when present) will help prevent these cardiac complications and will increase the effectiveness of agents administered to restore normal cardiac function.
In addition to the use of a narcotic antagonist, the patient may require careful titration with an anticonvulsant to control convulsions. Analeptic drugs (for example, caffeine or amphetamine) should not be used because of their tendency to precipitate convulsions.
General supportive measures, in addition to oxygen, include, when necessary, intravenous fluids, vasopressor-inotropic compounds, and, when infection is likely, anti-infective agents. Gastric lavage may be useful, and activated charcoal can adsorb a significant amount of ingested propoxyphene. Dialysis is of little value in poisoning due to propoxyphene. Efforts should be made to determine whether other agents, such as alcohol, barbiturates, tranquilizers, or other CNS depressants, were also ingested, since these increase CNS depression as well as cause specific toxic effects.

Symptoms of Acetaminophen Overdosage

Shortly after oral ingestion or an overdose of acetaminophen and for the next 24 hours, anorexia, nausea, vomiting, diaphoresis, general malaise, and abdominal pain have been noted. The patient may then present no symptoms, but evidence of liver dysfunction may become apparent up to 72 hours after ingestion, with elevated serum transaminase and lactic dehydrogenase levels, an increase in serum bilirubin concentrations, and a prolonged prothrombin time. Death from hepatic failure may result 3 to 7 days after overdosage.
Acute renal failure may accompany the hepatic dysfunction and has been noted in patients who do not exhibit signs of fulminant hepatic failure. Typically, renal impairment is more apparent 6 to 9 days after ingestion of the overdose.

Treatment of Acetaminophen Overdosage

Acetaminophen in massive overdosage may cause hepatic toxicity in some patients. In all cases of suspected overdose, immediately call your regional poison center or the Rocky Mountain Poison Center’s toll-free number (800-525-6115) for assistance in diagnosis and for directions in the use of N-acetylcysteine as an antidote.
In adults, hepatic toxicity has rarely been reported with acute overdoses of less than 10 g and fatalities with less than 15 g. Importantly, young children seem to be more resistant than adults to the hepatotoxic effect of an acetaminophen overdose. Despite this, the measures outlined below should be initiated in any adult or pediatric patients suspected of having ingested an acetaminophen overdose.
Because clinical and laboratory evidence of hepatic toxicity may not be apparent until 48 to 72 hours postingestion, liver function studies should be obtained initially and repeated at 24-hour intervals.
Consider emptying the stomach promptly by lavage or by induction of emesis with syrup of ipecac. Patients’ estimates of the quantity of a drug ingested are notoriously unreliable. Therefore, if an acetaminophen overdose is suspected, a serum acetaminophen assay should be obtained as early as possible, but no sooner than 4 hours following ingestion. The antidote, N-acetylcysteine, should be administered as early as possible, and within 16 hours of the overdose ingestion for optimal results. Following recovery, there are no residual, structural, or functional hepatic abnormalities.

HOW SUPPLIED

This product is given orally. The usual dosage is 100 mg propoxyphene napsylate and 650 mg acetaminophen every 4 hours as needed for pain. The maximum recommended dose of propoxyphene napsylate is 600 mg per day.
Consideration should be given to a reduced total daily dosage in patients with hepatic or renal impairment.

HOW SUPPLIED

Each pink Propoxyphene Napsylate and Acetaminophen Tablet USP 100 mg/650 mg is available as a capsule-shaped, pink, coated tablet, one side debossed M and the other side debossed “1772”.

Bottles of 15.......................................NDC 67296-0105-1

Dispense in tight containers. Store at 20° to 25°C (68° to 77°F) [see USP Controlled Room Temperature].

ANIMAL PHARMACOLOGY AND OR TOXICOLOGY

The acute lethal doses of the hydrochloride and napsylate salts of propoxyphene were determined in 4 species. The results shown in Figure 2 indicate that, on a molar basis, the napsylate salt is less toxic than the hydrochloride. This may be due to the relative insolubility and retarded absorption of propoxyphene napsylate.
Some indication of the relative insolubility and retarded absorption of propoxyphene napsylate was obtained by measuring plasma propoxyphene levels in 2 groups of 4 dogs following oral administration of equimolar doses of the 2 salts. As shown in Figure 3, the peak plasma concentration observed with propoxyphene hydrochloride was much higher than that obtained after administration of the napsylate salt.
Although none of the animals in this experiment died, 3 of the 4 dogs given propoxyphene hydrochloride exhibited convulsive seizures during the time interval corresponding to the peak plasma levels. The 4 animals receiving the napsylate salt were mildly ataxic but not acutely ill.
Figure 3. Plasma propoxyphene concentrations in dogs following large doses of the hydrochloride and napsylate salts.Mallinckrodt Inc.,
Hazelwood, MO 63042 USA.
Printed in U.S.A.

Label

copy of label